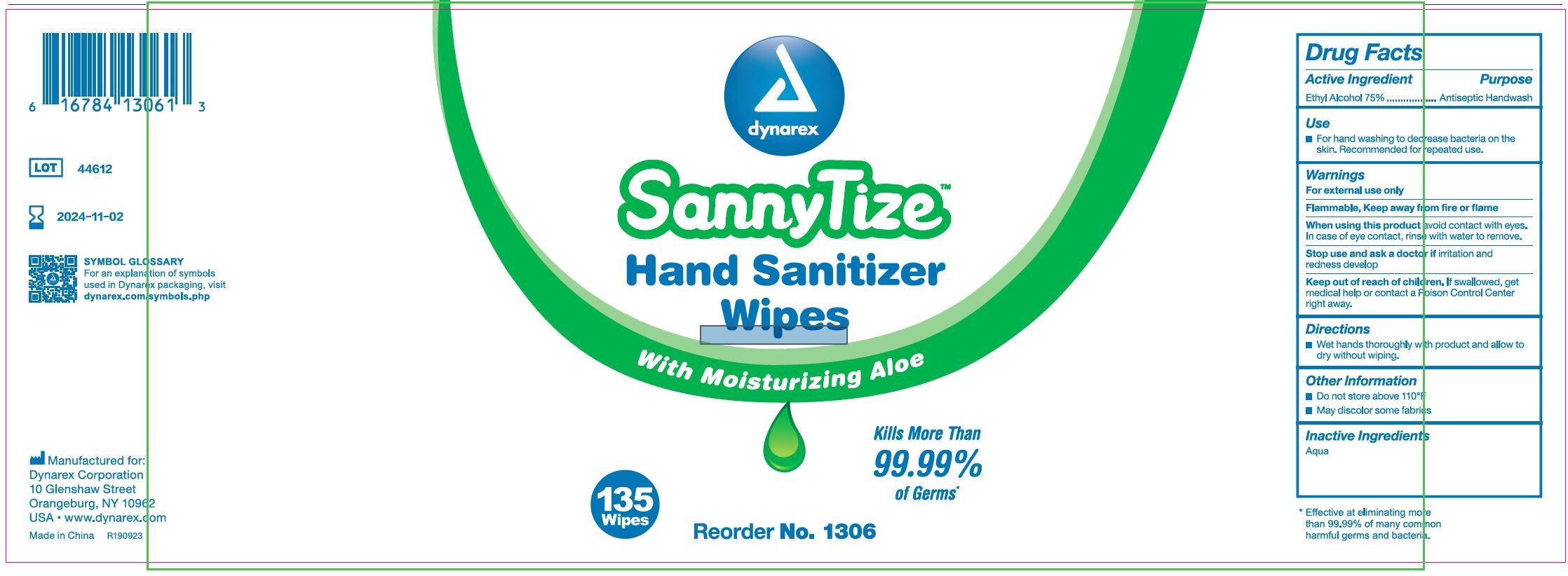 DRUG LABEL: Hand Sanitizer Wipes
NDC: 69821-006 | Form: CLOTH
Manufacturer: Zhejiang Qimei Commodity Co.,Ltd.
Category: otc | Type: HUMAN OTC DRUG LABEL
Date: 20221121

ACTIVE INGREDIENTS: ALCOHOL 70 mL/100 g
INACTIVE INGREDIENTS: WATER; ALOE VERA LEAF; CARBOMER HOMOPOLYMER, UNSPECIFIED TYPE; DIAZOLIDINYL UREA; GLYCERIN; PROPYLENE GLYCOL; PROPYLPARABEN; TROLAMINE; POLYSORBATE 20; ALPHA-TOCOPHEROL ACETATE; METHYLPARABEN

69821-006 70% Ethyl Alcohol Hand Sanitizer Wipes

Active ingredient

Ethyl Alcohol 70%

Purpose

Antiseptic Handwash

Uses

■ For hand washing to dec rease bacteria on the
skin. Recommended for repeated use.

Warnings

For external use only
Flammable, Keep away from fire or flame
When using this product avoid contact with eyes.
In case of eye contact, rins e with water to remove.
Stop use and ask a doctor if irritation and
redness develop

Keep out of reach of children. If swallowed, get
medical help or contact a Poison Control Center
right away.

Directions

■Wet hands thoroughly wi th product and allow to
dry without wiping.

INACTIVE INGREDIENT

Aloe Barbadensis Leaf Juice, Carbormer,Diazolidinyl Urea, Glycerin,Methylparaben,
Polysorbate 20, Propylene Glycol, Propylparaben,Tocopheryl Acetate, Trietha nolamine, Water